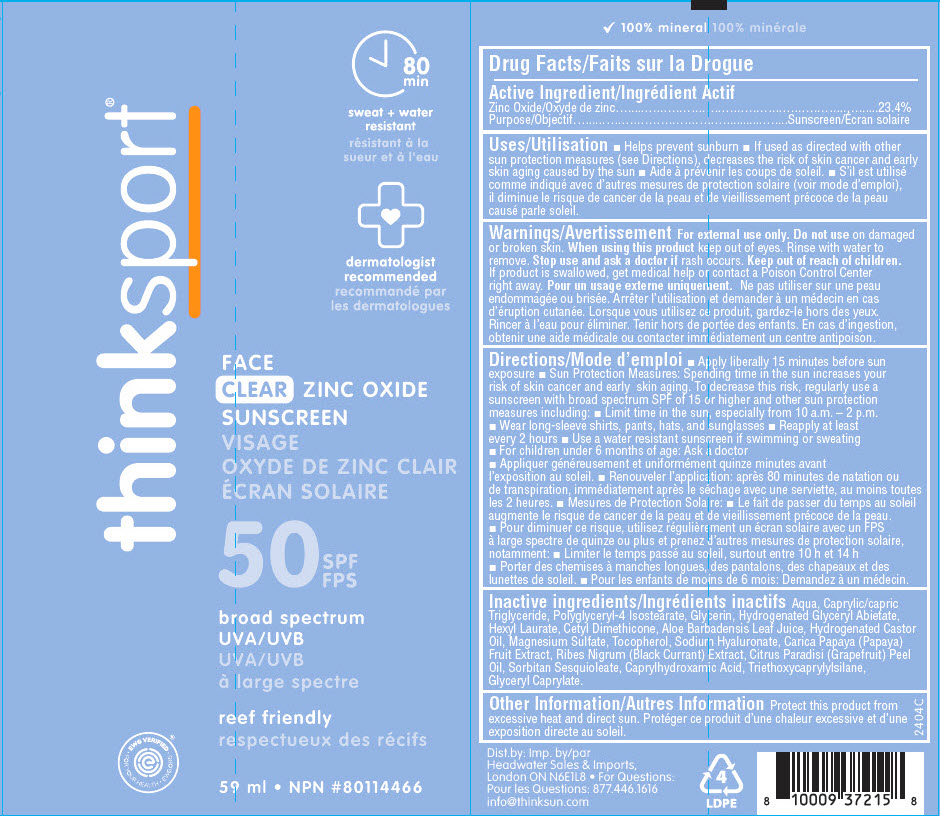 DRUG LABEL: Thinksport Daily Face
NDC: 60781-4421 | Form: LOTION
Manufacturer: thinkOperations,LLC
Category: otc | Type: HUMAN OTC DRUG LABEL
Date: 20240724

ACTIVE INGREDIENTS: ZINC OXIDE 234 mg/1 mL
INACTIVE INGREDIENTS: WATER; MEDIUM-CHAIN TRIGLYCERIDES; POLYGLYCERYL-4 ISOSTEARATE; GLYCERIN; GLYCERYL ABIETATE; HEXYL LAURATE; CETYL DIMETHICONE 150; ALOE VERA LEAF; HYDROGENATED CASTOR OIL; MAGNESIUM SULFATE ANHYDROUS; .ALPHA.-TOCOPHEROL; HYALURONATE SODIUM; PAPAYA; BLACK CURRANT; CITRUS PARADISI FRUIT OIL; SORBITAN SESQUIOLEATE; CAPRYLHYDROXAMIC ACID; TRIETHOXYCAPRYLYLSILANE; GLYCERYL MONOCAPRYLATE

Thinksport® Daily Face
SPF 50

Drug Facts

Active Ingredient

Zinc Oxide 23.4%

Purpose

Sunscreen

Uses

- Helps prevent sunburn
- If used as directed with other sun protection measures (see Directions), decreases the risk of skin cancer and early skin aging caused by the sun

Warnings

For external use only.

Do not use on damaged or broken skin.

When using this product keep out of eyes. Rinse with water to remove.

Stop use and ask a doctor if rash occurs.

Keep out of reach of children. If product is swallowed, get medical help or contact a Poison Control Center right away.

Directions

- Apply liberally 15 minutes before sun exposure
- Sun Protection Measures: Spending time in the sun increases your risk of skin cancer and early skin aging. To decrease this risk, regularly use a sunscreen with broad spectrum SPF of 15 or higher and other sun protection measures including:
  - Limit time in the sun, especially from 10 a.m. – 2 p.m.
  - Wear long-sleeve shirts, pants, hats, and sunglasses
  - Reapply at least every 2 hours
  - Use a water resistant sunscreen if swimming or sweating
  - For children under 6 months of age: Ask a doctor

Inactive ingredients

Aqua, Caprylic/capric Triglyceride, Polyglyceryl-4 Isostearate, Glycerin, Hydrogenated Glyceryl Abietate, Hexyl Laurate, Cetyl Dimethicone, Aloe Barbadensis Leaf Juice, Hydrogenated Castor Oil, Magnesium Sulfate, Tocopherol, Sodium Hyaluronate, Carica Papaya (Papaya) Fruit Extract, Ribes Nigrum (Black Currant) Extract, Citrus Paradisi (Grapefruit) Peel Oil, Sorbitan Sesquioleate, Caprylhydroxamic Acid, Triethoxycaprylylsilane, Glyceryl Caprylate.

Other Information

Protect this product from excessive heat and direct sun.

For Questions

877.446.1616

Dist.by:
Headwater Sales & Imports,
London ON N6E1L8

PRINCIPAL DISPLAY PANEL - 59 ml Tube Label

thinksport®

80
min
sweat + water
resistant

dermatologist
recommended

FACE
CLEAR ZINC OXIDE
SUNSCREEN

50 SPF

broad spectrum
UVA/UVB

reef friendly

• EWG VERIFIED •
FOR YOUR HEALTH • EWG.ORG

59 ml • NPN # 80114466